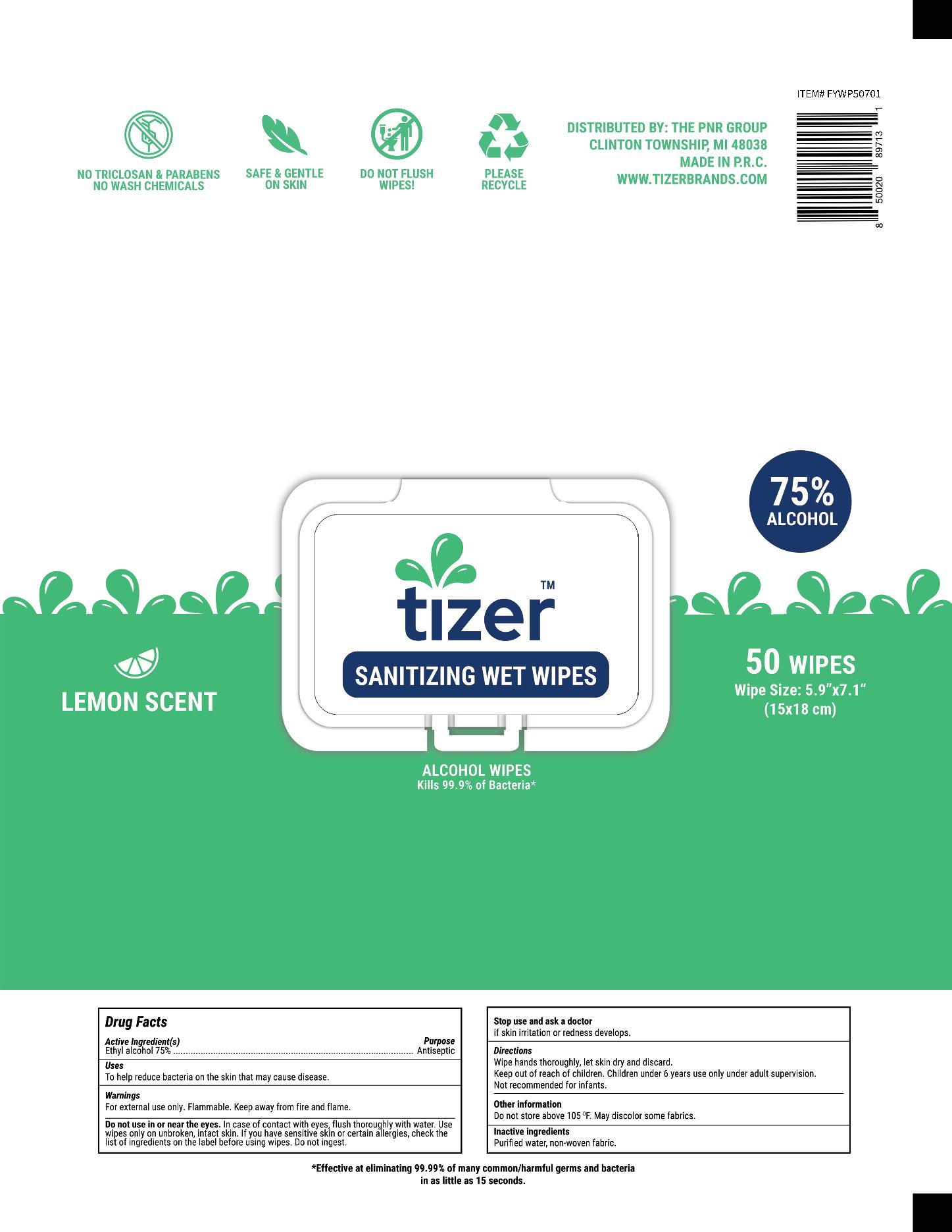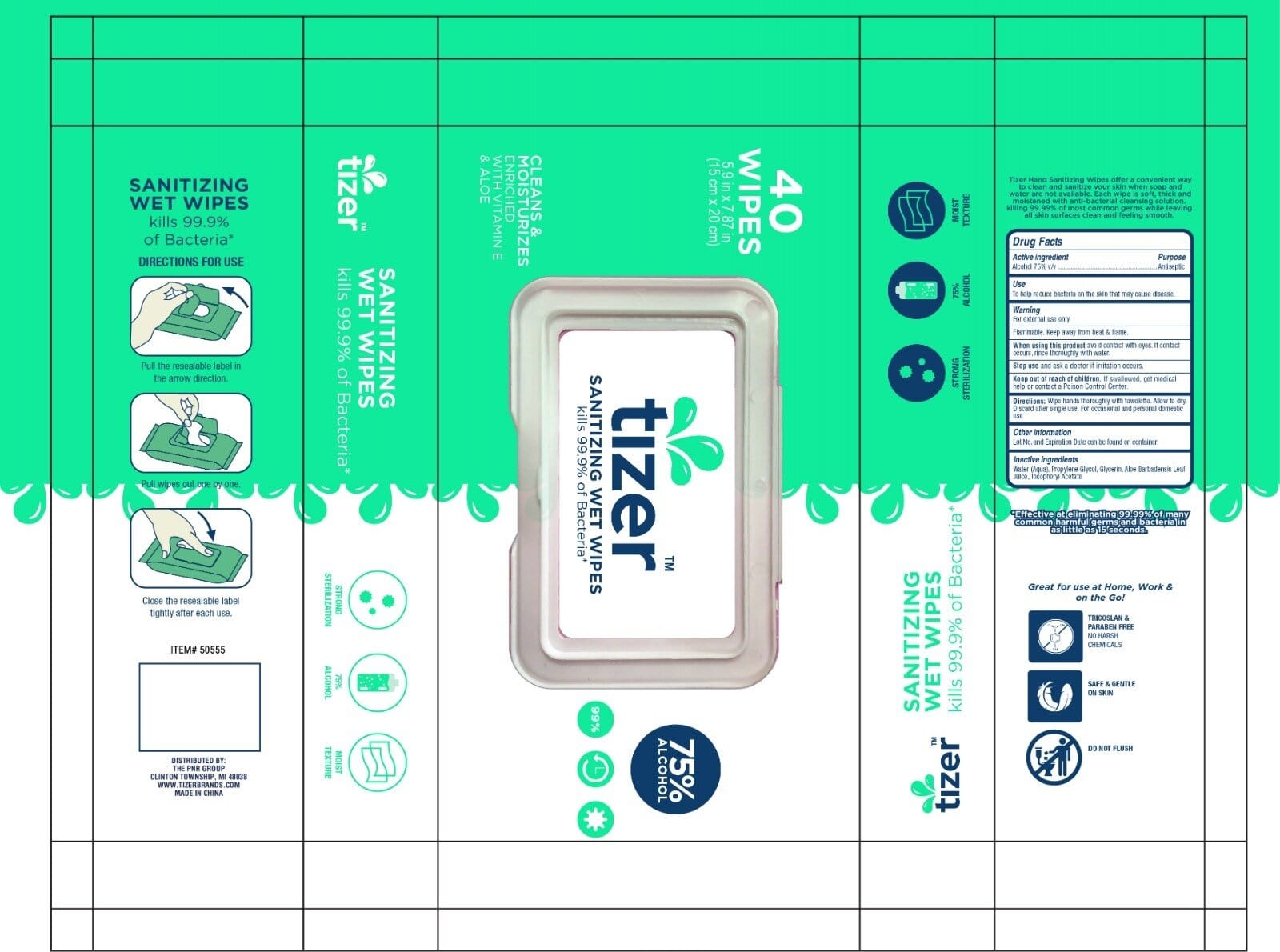 DRUG LABEL: Tizer Go Wipes
NDC: 80628-102 | Form: LIQUID
Manufacturer: The PnR Group, LLC
Category: otc | Type: HUMAN OTC DRUG LABEL
Date: 20200922

ACTIVE INGREDIENTS: ALCOHOL 80 mL/100 mL
INACTIVE INGREDIENTS: GLYCERIN; WATER; ALPHA-TOCOPHEROL ACETATE; PROPYLENE GLYCOL; ALOE VERA LEAF

Tizer Go

Active Ingredient(s)

Alcohol 80% v/v. Purpose: Antiseptic

Purpose

Antiseptic

Use

To help reduce bacteria on the skin that may cause disease.

Warnings

For external use only. Flammable. Keep away from heat or flame

Do not use

- in children less than 2 months of age
- on open skin wounds

When using this product keep out of eyes, ears, and mouth. In case of contact with eyes, rinse eyes thoroughly with water.

Stop use and ask a doctor if irritation occurs.

Keep out of reach of children. If swallowed, get medical help or contact a Poison Control Center right away.

Directions

Wipe hands thoroughly with towelette. Allow to dry. Discard after single use. For occasional and personal domestic use.

Other information

Lot No. and Expiration Date can be found on container.

Inactive ingredients

Water (Aqua), Propylene Glycol, Glycerin, Aloe Barbadensis Leaf Juice, Tocopheryl Acetate